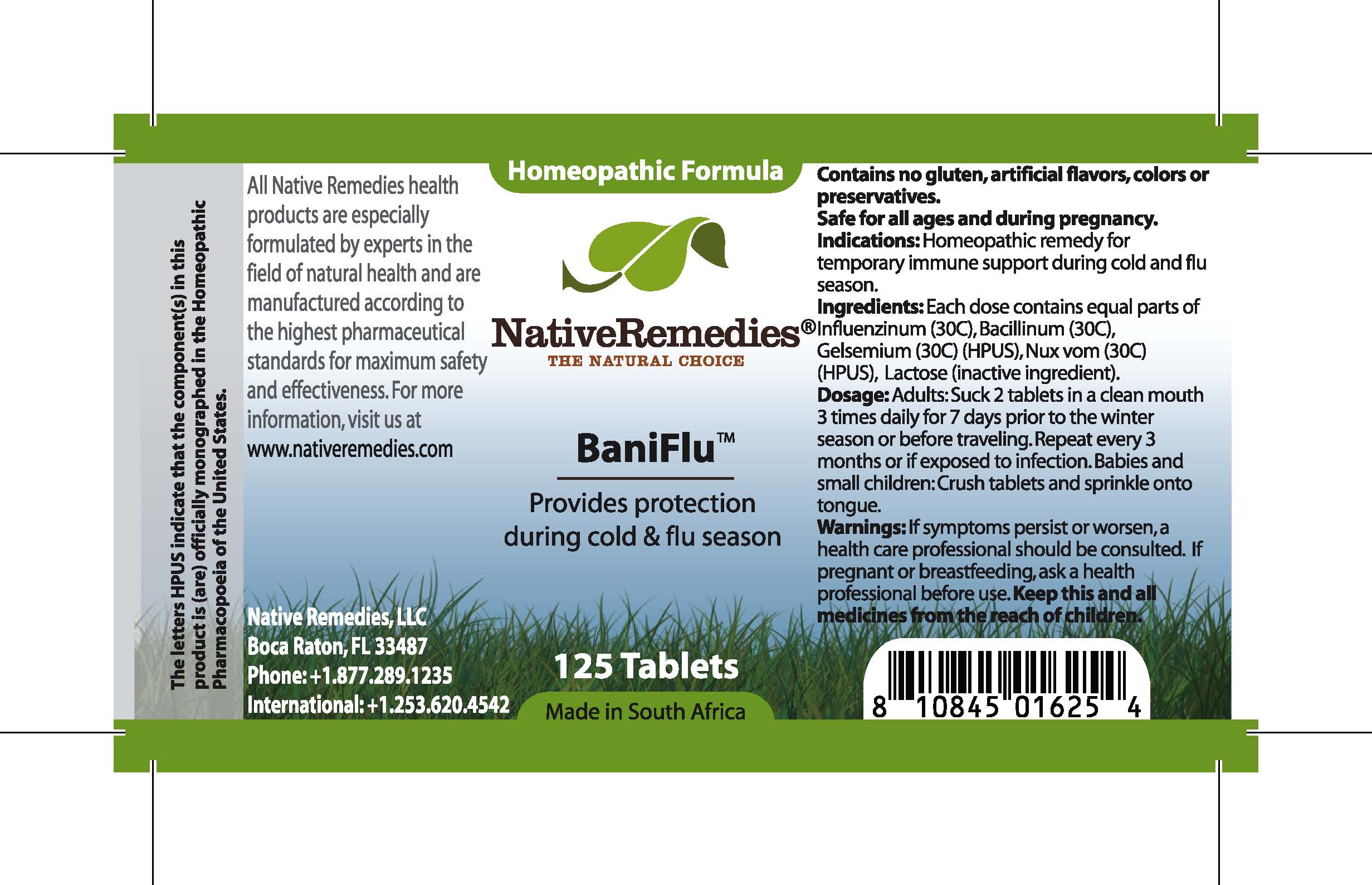 DRUG LABEL: BaniFlu
NDC: 68647-120 | Form: TABLET
Manufacturer: Feelgood Health
Category: homeopathic | Type: HUMAN OTC DRUG LABEL
Date: 20100717

ACTIVE INGREDIENTS: HAEMOPHILUS INFLUENZAE TYPE B 30 [hp_C]/1 1; ESCHERICHIA COLI 30 [hp_C]/1 1; GELSEMIUM SEMPERVIRENS ROOT 30 [hp_C]/1 1
INACTIVE INGREDIENTS: LACTOSE

BANIFLU

DESCRIPTION

Provides protection during cold and flu season

INDICATIONS AND USAGE

Indications: Homeopathic remedy for immune support during cold and flu season.

DOSAGE AND ADMINISTRATION

Dosage: Adults: Dissolve 2 tablets in a clean mouth 3 times daily for 7 days prior to the winter season or before traveling. Repeat every 3 months or if exposed to infection. Babies and small children: Crush tablets and sprinkle onto tongue.

GENERAL PRECAUTIONS

Caution: If symptoms persist or worsen, a health care professional should be consulted.Keep this and all medicines from the reach of children.

ACTIVE INGREDIENT

Ingredients: Each dose contains equal parts of Influenzinum (30C), Bacillinum (30C), Gelsemium (30C) (HPUS), Nux vom (30C) (HPUS)

Lactose (inactive ingredient).

PREGNANCY

If pregnant or breastfeeding, ask a health professional before use.

USER SAFETY WARNINGS

Contains no gluten, artificial flavors, colors or preservatives. Safe for all ages and during pregnancy.

PATIENT COUNSELING INFORMATION

All Native Remedies health products are especially formulated by experts in the field of natural health and are manufactured according to the highest pharmaceutical standards for maximum safety and effectiveness. For more information, visit us at www.nativeremedies.com

Distributed by

Native Remedies, LLC

6531 Park of Commerce Blvd.

Suite 160

Boca Raton, FL 33487

Phone: +1.877.289.1235

International: +1.561.999.8857

The letters HPUS indicate that the component(s) in this product is (are) officially monographed in the Homeopathic Pharmacopoeia of the United States.